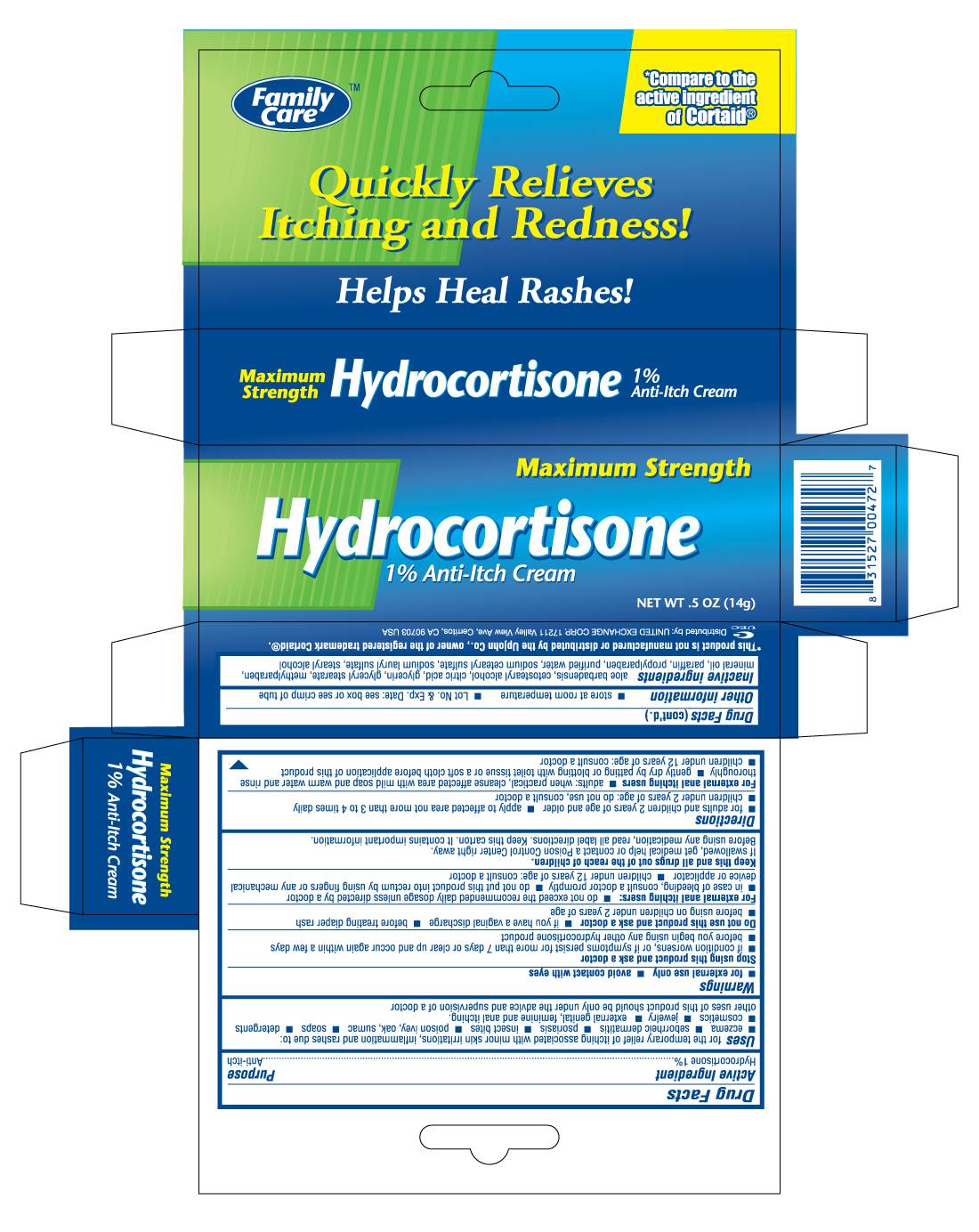 DRUG LABEL: FAMILY CARE HYDROCORTISONE
NDC: 65923-472 | Form: CREAM
Manufacturer: UNITED EXCHANGE CORP.
Category: otc | Type: HUMAN OTC DRUG LABEL
Date: 20120401

ACTIVE INGREDIENTS: HYDROCORTISONE 1 g/100 g
INACTIVE INGREDIENTS: CETOSTEARYL ALCOHOL; CITRIC ACID MONOHYDRATE; GLYCERIN; GLYCERYL MONOSTEARATE; METHYLPARABEN; MINERAL OIL; PROPYLPARABEN; WATER; SODIUM CETOSTEARYL SULFATE; STEARYL ALCOHOL

Drug Facts

Active ingredient Purpose

Hydrocortisone 1%....................................................................Anti-itch

PURPOSE

Uses for the temporary relief of itching associated with minor skin irriations, inflammation and rashes due to:

- eczema
- seborrheic dermatitis
- psoriasis
- insect bites
- poison ivy, oak, sumac
- soaps
- detergents
- cosmetics
- jewelry
- external genital, feminine and anal itching.

Other uses or the use of the product for more than 7 days should be undertaken only under the advice and supervision of a doctor

Warnings

- for external use only
- avoid contact with eyes

Stop using this product and ask a doctor

- if condition worsens, or if symptoms persist for more than 7 days or clear up and occur again within a few days
- before you begin using any other hydrocortisone product

Do not use this product and ask a doctor

- if you have a vaginal discharge
- before treating diaper rash
- before using on children under 2 years of age

KEEP OUT OF REACH OF CHILDREN

Keep this and all drugs out of the reach of children.

If swallowed, get medical help or contact a Poison Control Center right away.

Before using any medication, read all label directions. Keep this carton. It contains important information.

Directions

- for adults and children 2 years of age and older: apply to affected area not more than 3 to 4 times daily
- children under 2 years of age: do not use, consult a doctor

Other information

- store at room temperature
- Lot No. and Exp. Date: see box or see crimp of tube

Inactive ingredients

glycerin, propylene glycol, sodium chloride, white petrolatum, cetyl alcohol, dimethicone, isopropyl palmitate, distearyldimonium chloride, methylparaben, propylparaben, purified water

DOSAGE AND ADMINISTRATION

Distributed By:

UNITED EXCHANGE CORP.

17211 Valley View Ave.

Cerritos, CA 90703 USA

Made in Korea

PACKAGE LABEL

Enter section text here